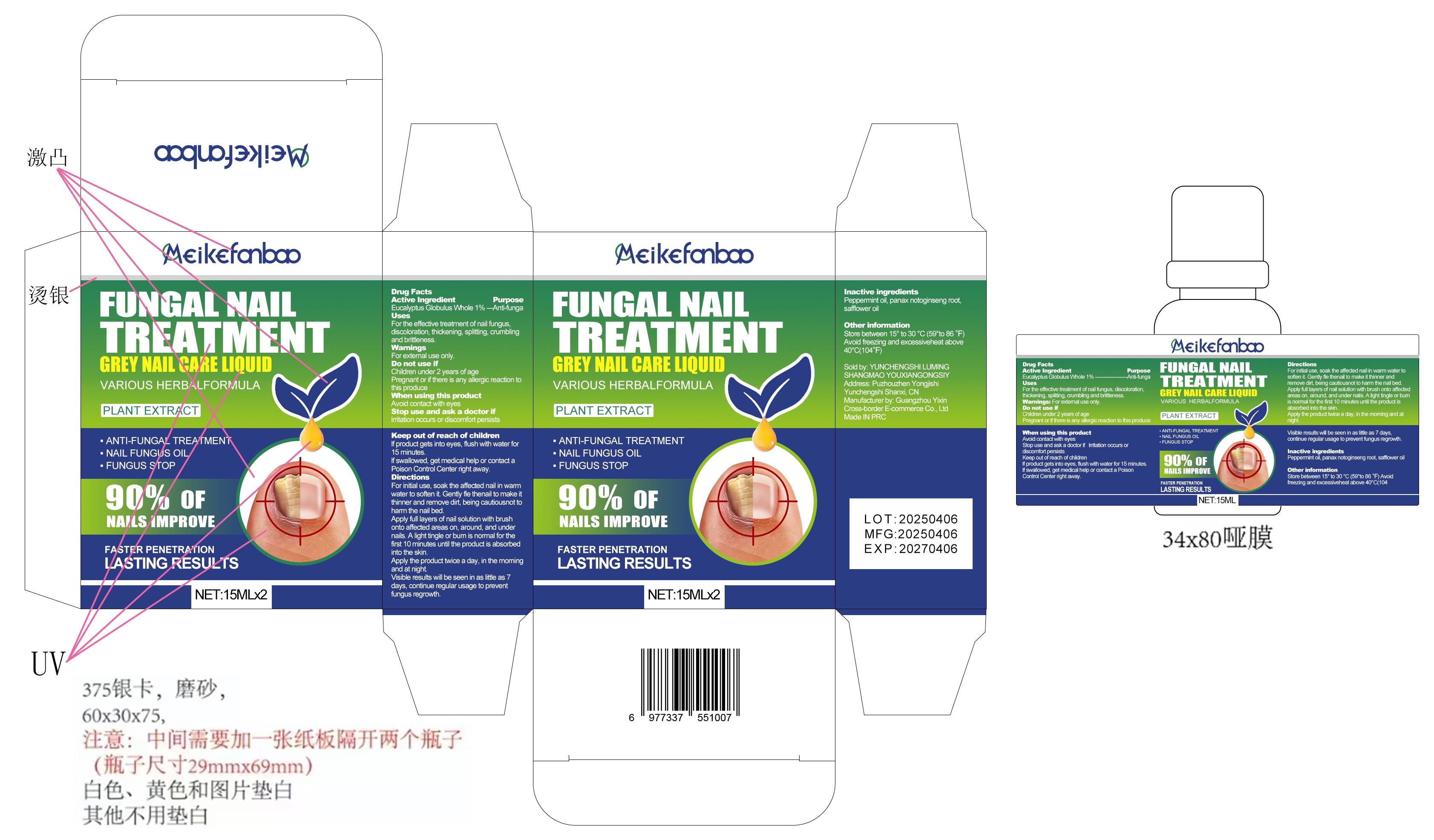 DRUG LABEL: Fungal Nail Treatment
NDC: 84778-075 | Form: LIQUID
Manufacturer: Guangzhou Yixin Cross-border E-commerce Co., Ltd.
Category: otc | Type: HUMAN OTC DRUG LABEL
Date: 20250701

ACTIVE INGREDIENTS: EUCALYPTUS GLOBULUS WHOLE 1 g/100 g
INACTIVE INGREDIENTS: PEPPERMINT OIL; PANAX NOTOGINSENG ROOT; SAFFLOWER OIL

Active ingredients

Eucalyptus Globulus Whole 1%

Purpose

Anti-funga

Uses

For the effective treatment of nail fungus, discoloration, thickening, splitting, crumbling and brittleness

Warnings

For external use only.

Dosage and administration

For initial use, soak the affected nail in warm water to soften it. Gently fle thenail to make it thinner and remove dirt, being cautiousnot to harm the nail bed.

Apply full layers of nail solution with brush onto affected areas on, around, and under nails. A light tingle or burn is normal for the first 10 minutes until the product is absorbed into the skin.

Apply the product twice a day, in the morning and at night.

Visible results will be seen in as little as 7 days, continue regular usage to prevent fungus regrowth.

Do not use

Children under 2 years of age

pregnant or if there is any allergic reaction to this produce

When using section

Avoid contact with eyes

stop use

lrritation occurs or discomfort persists

Keep out of reach of children.

lf product gets into eyes, flush with water for 15 minutes.

lf swallowed, get medical help or contact a Poison Control Center right away.

Inactive ingredients

Peppermint oil, SAFFLOWER OIL, NOTOGINSENG RADIX